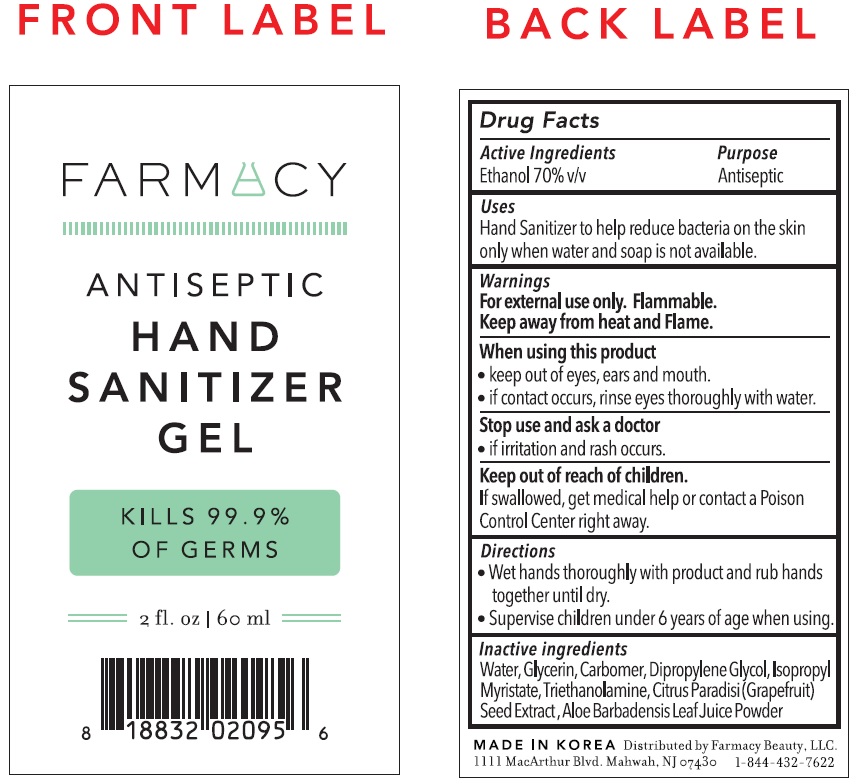 DRUG LABEL: Farmacy Antiseptic Hand Sanitizer
NDC: 72830-001 | Form: GEL
Manufacturer: Farmacy Beauty LLC
Category: otc | Type: HUMAN OTC DRUG LABEL
Date: 20200420

ACTIVE INGREDIENTS: ALCOHOL 0.7 mL/1 mL
INACTIVE INGREDIENTS: WATER; GLYCERIN; CARBOMER HOMOPOLYMER, UNSPECIFIED TYPE; DIPROPYLENE GLYCOL; ISOPROPYL MYRISTATE; TROLAMINE; CITRUS PARADISI SEED; ALOE VERA LEAF

Farmacy Antiseptic Hand Sanitizer Gel

Active Ingredients

Ethanol 70% v/v

Purpose

Antiseptic

Uses

Hand Santizer to help reduce bacteria on the skin only when water and soap is not availabel.

Warnings

For external use only. Flammable. Keep away from heat and Flame.

When using this product

- keep out of eyes, ears and mouth.
- if contact occurs, rinse eyes thorughly with water.

Stop use and ask a doctor

- if irritation and rash occurs.

Keep out of reach of children.

If swallowed, get medical help or contact a Poison Control Center right away.

Directions

- Wet hands thoroughly with product and rub hands together until dry.
- Supervise children under 6 years of age when using.

Inactive Ingredients

Water, Glycerin, Carbomer, Dipropylene Glycol, Isopropyl Myristate, Triethanolamine, Citrus Paradisi (Grapefruit) Seed Extract, Aloe Barbadensis Leaf Juice Powder